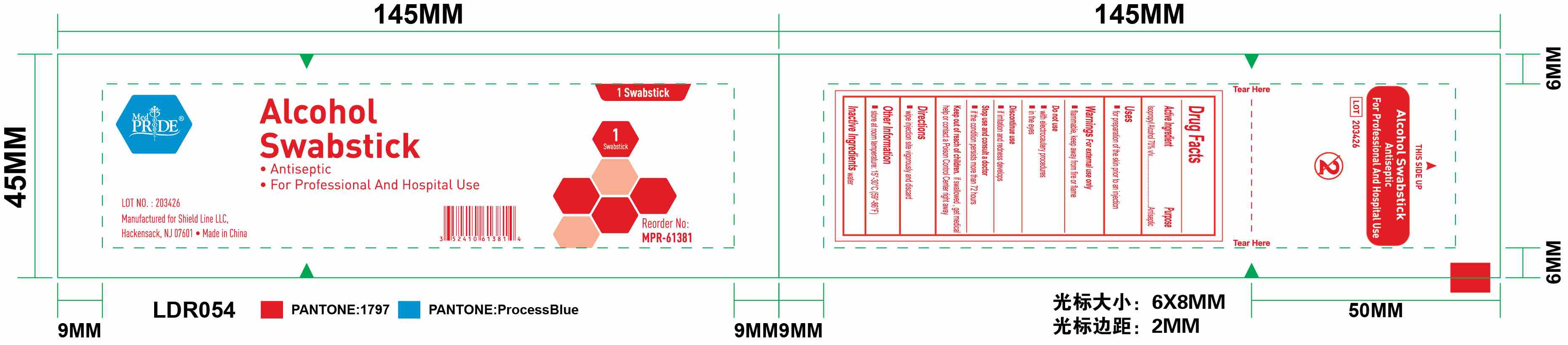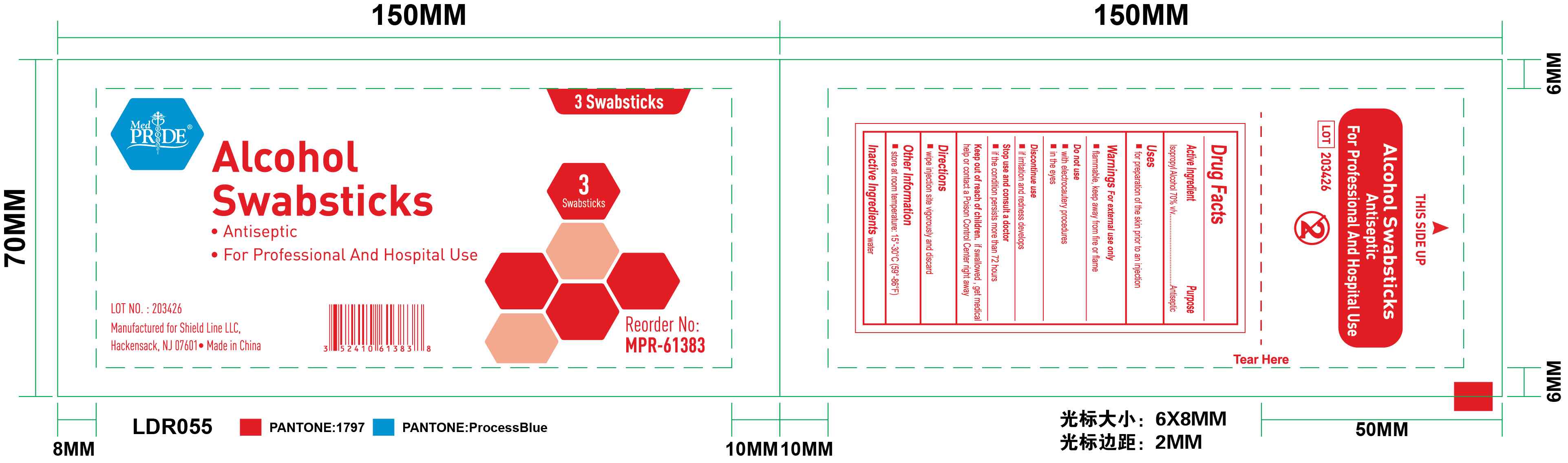 DRUG LABEL: Alcohol Swabstick - Antiseptic
NDC: 49953-1801 | Form: SWAB
Manufacturer: Dalian Rongbang Medical Healthy Devices Co., Ltd.
Category: otc | Type: HUMAN OTC DRUG LABEL
Date: 20231228

ACTIVE INGREDIENTS: ISOPROPYL ALCOHOL 0.7 mL/1 mL
INACTIVE INGREDIENTS: WATER

Alcohol Swabsticks - Antiseptic

ACTIVE INGREDIENT

70% Isopropyl Alcohol

PURPOSE

Antiseptic

USE

- For preparation of the skin prior to an injection

WARNINGS

- For external use only
- Flammable, keep away from fire or flame

Do not use

- with electrocautery procedures
- in the eyes

Discontinue use

- if irritation and redness develops

Stop use and consult a doctor

- if the condition persists for more than 72 hours

Keep out of reach of children. If swallowed, get medical help or contact a Poison Control Center right away.

DIRECTIONS

- wipe injection site vigorously and discard

Other Information

- Store at room temperature: 15o-30o C (59o-86o F)

INACTIVE INGREDIENT

Water